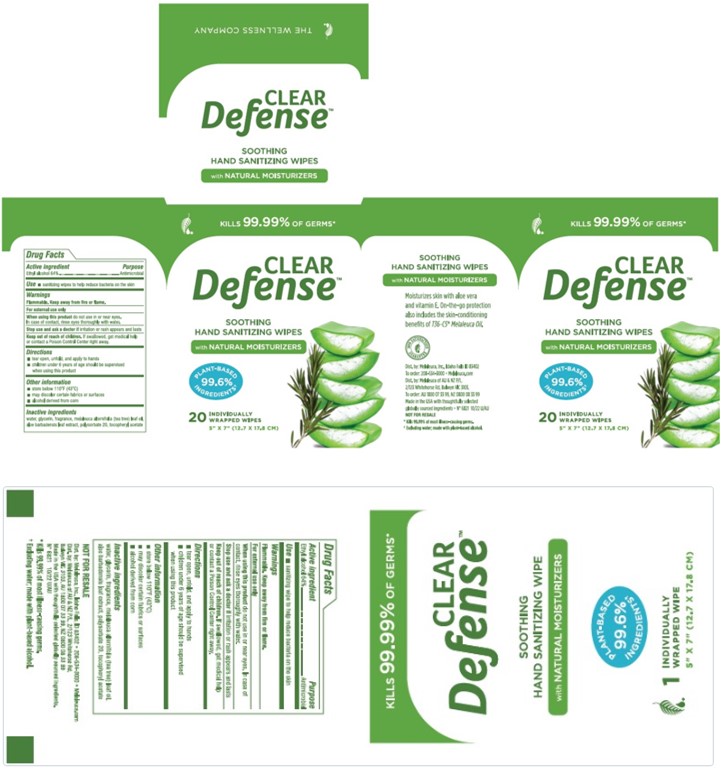 DRUG LABEL: Clear Defense
NDC: 54473-409 | Form: CLOTH
Manufacturer: Melaleuca, Inc.
Category: otc | Type: HUMAN OTC DRUG LABEL
Date: 20250424

ACTIVE INGREDIENTS: ALCOHOL 3.32 g/1 1
INACTIVE INGREDIENTS: WATER; ALPHA-TOCOPHEROL ACETATE; ALOE VERA LEAF; MELALEUCA ALTERNIFOLIA (TEA TREE) LEAF OIL; POLYSORBATE 20; GLYCERIN

Clear Defense Wipes

Active Ingredient

Ethyl alcohol 64%

Purpose

Antimicrobial

Use

- sanitizing wipes to help reduce bacteria on the skin

Warnings

Flammable. Keep away from fire or flame.

For external use only

When using this product do not use in or near eyes.

In case of contact, rinse eyes thoroughly with water.

Stop use and ask a doctor if irritation or rash appears and lasts

Keep out of reach of children. If swallowed, get medical help or contact a Poison Control Center right away.

Directions

- Tear open, unfold, and apply to hands
- children under 6 years of age should be supervised when using this product

Other information

- store below110°F (43°C)

Other information

- may discolor certain fabrics or surfaces
- alcohol derived from corn

Inactive ingredients

water, glycerin, fragrance, melaleuca alternifolia (tea tree) leaf oil, aloe barbadensis leaf extract, polysorbate 20, tocopheryl acetate